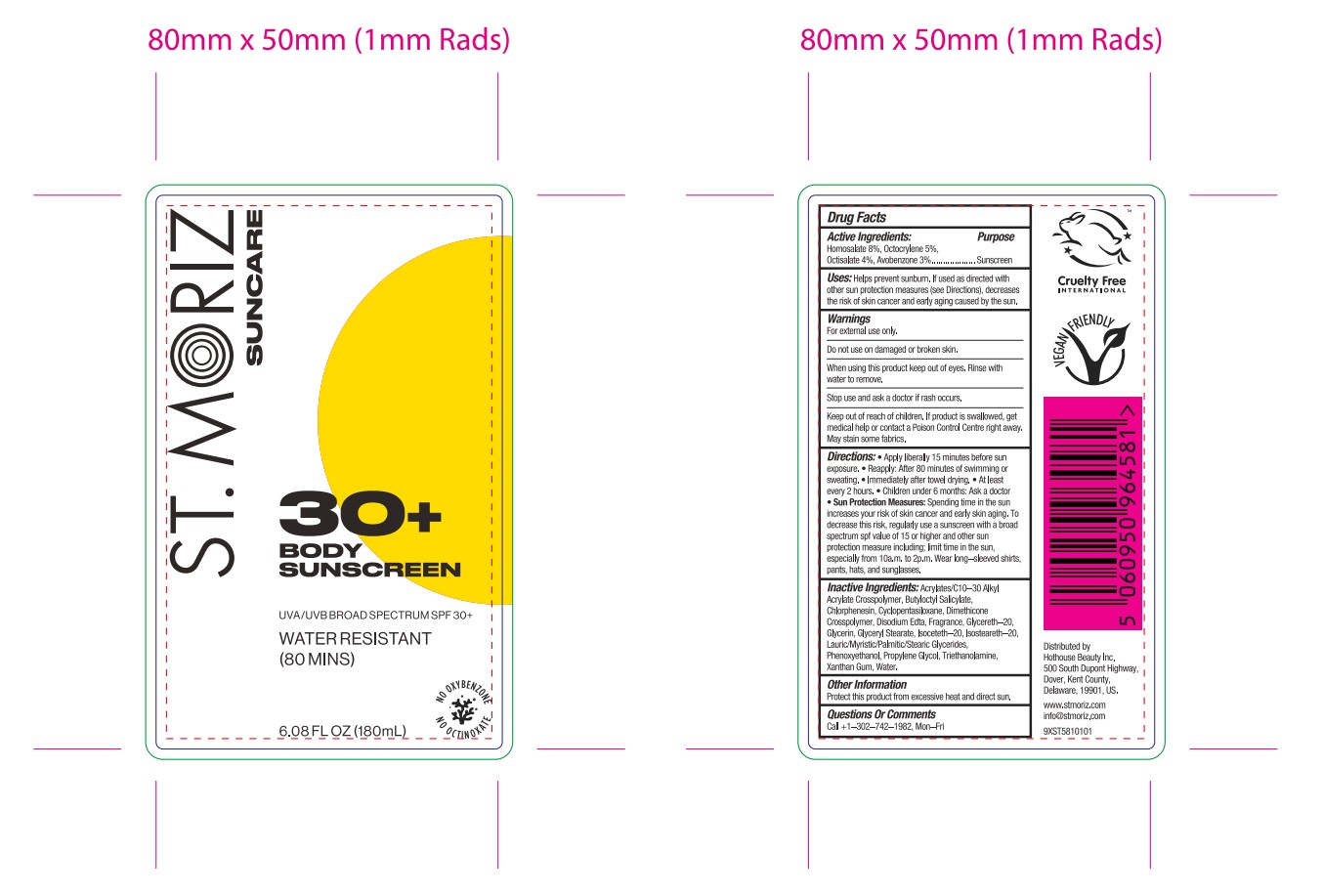 DRUG LABEL: St Moriz suncare body sunscreen spf30
NDC: 82723-013 | Form: LOTION
Manufacturer: Aopline Health Industry Technology (Guangzhou) Co., Ltd.
Category: otc | Type: HUMAN OTC DRUG LABEL
Date: 20250126

ACTIVE INGREDIENTS: HOMOSALATE 14.4 mg/180 mL; GLYCERIN 10.9 mg/180 mL; OCTOCRYLENE 9 mg/180 mL; AVOBENZONE 5.4 mg/180 mL; OCTISALATE 7.2 mg/180 mL
INACTIVE INGREDIENTS: PROPYLENE GLYCOL; GLYCERYL STEARATE; PHENOXYETHANOL; EDETATE DISODIUM; ALUMINUM STARCH OCTENYLSUCCINATE; WATER; GLYCERETH-20; TRIETHANOLAMINE; CHLORPHENESIN; XANTHAN GUM; BUTYLOCTYL SALICYLATE; ISOSTEARETH-20; ISOCETETH-20; LAURIC ACID; ACRYLATES/C10-30 ALKYL ACRYLATE CROSSPOLYMER (60000 MPA.S)

Active ingredient

HOMOSALATE
GLYCERIN
OCTOCRYLENE
OCTISALATE
AVOBENZONE

Inactive ingredient

PROPYLENE GLYCOL
WATER
BUTYLOCTYL SALICYLATE
GLYCERETH-20
ISOSTEARETH-20
ISOCETETH-20
LAURIC/MYRISTIC/PALMITIC/STEARIC GLYCERIDES
GLYCERYL STEARATE
ALUMINUM STARCH OCTENYLSUCCINATE
PHENOXYETHANOL
ACRYLATES/C10-30 ALKYL ACRYLATE CROSSPOLYMER
TRIETHANOLAMINE
CHLORPHENESIN
FRAGRANCE
DISODIUM EDTA
XANTHAN GUM

PURPOSE

Helps prevent sunbum, if used as directed withother sun protection measures (see Direciions), decreasesthe risk of skin cancer and eary aging caused by the sun

Warning

For extemal use onl,.
Do not use on damaged or broken skn,
When using this product keep out of cyes, Rinse withwater to remowe,
Siop use and ask a doctor if rash cccurs.Keep out of reach of children, lf product is swalkawed, getmedical help or contact a Potson Conirol Centre right away.Wlay stain some fabrics.

stop to use

Stop use and ask a doctor if rash occurs

Do not use on damaged or broken skn

When

Apply liberaly 15 minues before sunexposure,

Reapply: After 80 minutes of swimming orsseating,

lmmedabely after touel drying.. At leastevery 2 hours,

keep out of children to use it

Indication

Directions: Apply liberaly 15 minues before sunexposure,

Reapply: After 80 minutes of swimming or sseating,

lmmedabely after towel drying.

At least every 2 hours,

Children under 6 months: Ask a Doctor

Sun Protection Measures: spendng time in the suni ncreases your risk of skin caner and early skin aging.

To decrease this risk, regulary use a sunsereen with a broad spectrum spf value of 15 or higher and other sun protection measure including, lmit time in the sun,especially from 10a,m. to 2p.m, Wear long-sleeved shirtspanis, hats, and sunglasses,

DOSAGE AND ADMINISTRATION

Directions: Apply liberaly 15 minues before sunexposure, e Reapply: After 80 minutes of swimming or seating,. lmmedabely after touel drying.. At leastevery 2 hours,